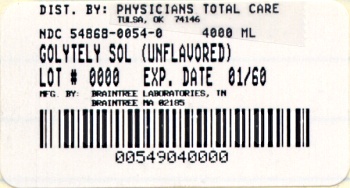 DRUG LABEL: GoLYTELY
NDC: 54868-0054 | Form: POWDER, FOR SOLUTION
Manufacturer: Physicians Total Care, Inc.
Category: prescription | Type: HUMAN PRESCRIPTION DRUG LABEL
Date: 20110802

ACTIVE INGREDIENTS: POLYETHYLENE GLYCOL 3350 236 g/2 L; SODIUM SULFATE ANHYDROUS 22.74 g/2 L; SODIUM BICARBONATE 6.74 g/2 L; SODIUM CHLORIDE 5.86 g/2 L; POTASSIUM CHLORIDE 2.97 g/2 L
INACTIVE INGREDIENTS: WATER

BRAINTREE LABORATORIES
GoLYTELY

DESCRIPTION

A white powder in a 4 liter jug for reconstitution, containing 236 g polyethylene glycol 3350, 22.74 g sodium sulfate (anhydrous), 6.74 g sodium bicarbonate, 5.86 g sodium chloride and 2.97 g potassium chloride. When dissolved in water to a volume of 4 liters, GoLYTELY for Oral Solution is an isosmotic solution having a mildly salty taste. GoLYTELY for Oral Solution is administered orally or via nasogastric tube as a gastrointestinal lavage.

CLINICAL PHARMACOLOGY

GoLYTELY for Oral Solution induces a diarrhea which rapidly cleanses the bowel, usually within four hours. The osmotic activity of polyethylene glycol 3350 and the electrolyte concentration result in virtually no net absorption or excretion of ions or water. Accordingly, large volumes may be administered without significant changes in fluid or electrolyte balance.

INDICATIONS AND USAGE

GoLYTELY for Oral Solution is indicated for bowel cleansing prior to colonoscopy and barium enema X-ray examination.

CONTRAINDICATIONS

GoLYTELY for Oral Solution is contraindicated in patients known to be hypersensitive to any of the components. GoLYTELY for Oral Solution is contraindicated in patients with gastrointestinal obstruction, gastric retention, bowel perforation, toxic colitis, toxic megacolon or ileus.

WARNINGS

No additional ingredients, e.g. flavorings, should be added to the solution. GoLYTELY for Oral Solution should be used with caution in patients with severe ulcerative colitis.

PRECAUTIONS:

GENERAL PRECAUTIONS

General: Patients with impaired gag reflex, unconscious, or semiconscious patients, and patients prone to regurgitation or aspiration should be observed during the administration of GoLYTELY for Oral Solution, especially if it is administered via nasogastric tube. If a patient experiences severe bloating, distention or abdominal pain, administration should be slowed or temporarily discontinued until the symptoms abate. If gastrointestinal obstruction or perforation is suspected, appropriate studies should be performed to rule out these conditions before administration of GoLYTELY for Oral Solution.

PATIENT COUNSELING INFORMATION

Information for patients: GoLYTELY for Oral Solution produces a watery stool which cleanses the bowel before examination. Prepare the solution according to the instructions on the bottle. It is more palatable if chilled. For best results, no solid food should be consumed during the 3 to 4 hour period before drinking the solution, but in no case should solid foods be eaten within 2 hours of taking GoLYTELY for Oral Solution.

Drink 240 mL (8 oz.) every 10 minutes. Rapid drinking of each portion is better than drinking small amounts continuously. The first bowel movement should occur approximately one hour after the start of GoLYTELY for Oral Solution administration. You may experience some abdominal bloating and distention before the bowels start to move. If severe discomfort or distention occur, stop drinking temporarily or drink each portion at longer intervals until these symptoms disappear. Continue drinking until the watery stool is clear and free of solid matter. This usually requires at least 3 liters and it is best to drink all of the solution. Any unused portion should be discarded.

DRUG INTERACTIONS

Drug Interactions: Oral medication administered within one hour of the start of administration of GoLYTELY for Oral Solution may be flushed from the gastrointestinal tract and not absorbed.

CARCINOGENESIS AND MUTAGENESIS AND IMPAIRMENT OF FERTILITY

Carcinogenesis, Mutagenesis, Impairment of Fertility: Carcinogenic and reproductive studies with animals have not been performed.

PREGNANCY

Pregnancy: Category C. Animal reproduction studies have not been conducted with GoLYTELY for Oral Solution. It is also not known whether GoLYTELY for Oral Solution can cause fetal harm when administered to a pregnant woman or can affect reproductive capacity. GoLYTELY for Oral Solution should be given to a pregnant woman only if clearly needed. Pediatric Use: Safety and effectiveness in children have not been established.

ADVERSE REACTIONS:

Nausea, abdominal fullness and bloating are the most common adverse reactions (occurring in up to 50% of patients) to administration of GoLYTELY for Oral Solution. Abdominal cramps, vomiting and anal irritation occur less frequently. These adverse reactions are transient and subside rapidly. Isolated cases of urticaria, rhinorrhea, dermatitis and (rarely) anaphylactic reaction have been reported which may represent allergic reactions.

Published literature contains isolated reports of serious adverse reactions following the administration of PEG-ELS products in patients over 60 years of age. These adverse events include upper GI bleeding from Mallory-Weiss Tear, esophageal perforation, asystole, sudden dyspnea with pulmonary edema, and “butterfly-like” infiltrates on chest X-ray after vomiting and aspirating PEG.

DOSAGE AND ADMINISTRATION:

The recommended dose for adults is 4 liters of GoLYTELY for Oral Solution solution prior to gastrointestinal examination, as ingestion of this dose produces a satisfactory preparation in over 95% of patients. Ideally, the patient should fast for approximately three or four hours prior to GoLYTELY for Oral Solution administration, but in no case should solid food be given for at least two hours before the solution is given.

GoLYTELY for Oral Solution is usually administered orally, but may be given via nasogastric tube to patients who are unwilling or unable to drink the solution. Oral administration is at a rate of 240 mL (8 oz.) every 10 minutes, until 4 liters are consumed or the rectal effluent is clear. Rapid drinking of each portion is preferred to drinking small amounts continuously. Nasogastric tube administration is at the rate of 20-30 mL per minute (1.2-1.8 liters per hour). The first bowel movement should occur approximately one hour after the start of GoLYTELY for Oral Solution administration.

Various regimens have been used. One method is to schedule patients for examination in midmorning or later, allowing the patients three hours for drinking and an additional one hour period for complete bowel evacuation. Another method is to administer GoLYTELY for Oral Solution on the evening before the examination, particularly if the patient is to have a barium enema.

Preparation of the solution: GoLYTELY for Oral Solution solution is prepared by filling the container to the 4 liter mark with water and shaking vigorously several times to ensure that the ingredients are dissolved. Dissolution is facilitated by using lukewarm water. The solution is more palatable if chilled before administration. The reconstituted solution should be refrigerated and used within 48 hours. Discard any unused portion.

HOW SUPPLIED

In powdered form, for oral administration as a solution following reconstitution.

GoLYTELY for Oral Solution is available in a disposable jug in powdered form containing:

Disposable Jug: polyethylene glycol 3350 236 g, sodium sulfate (anhydrous) 22.74 g, sodium bicarbonate 6.74 g, sodium chloride 5.86 g, potassium chloride 2.97 g. When made up to 4 liters volume with water, the solution contains PEG-3350 17.6 mmol/L, sodium 125 mmol/L, sulfate 40 mmol/L, chloride 35 mmol/L, bicarbonate 20 mmol/L and potassium 10 mmol/L (NDC 54868-0054-0).

STORAGE

Store in sealed container at 59°-86°F. When reconstituted, keep solution refrigerated. Use within 48 hours. Discard unused portion.

GoLYTELY for Oral Solution | NDC 54868-0054-0
Distributed by Braintree Laboratories, Inc., Braintree, MA 02185 Relabeling of "Additional Barcode Label" by: Physicians Total Care, Inc., Tulsa, OK 74146 | A 11/00

PACKAGE LABEL – PRINCIPAL DISPLAY PANEL

GoLYTELY for Oral Solution

Rx Only

NDC 54868-0054-0